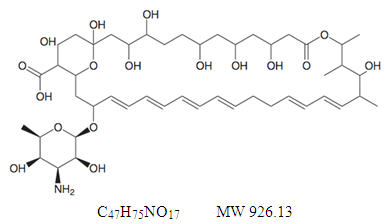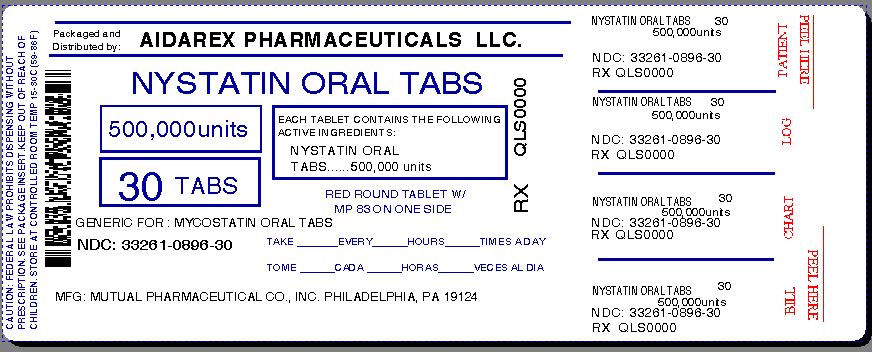 DRUG LABEL: Nystatin
NDC: 33261-896 | Form: TABLET, FILM COATED
Manufacturer: Aidarex Pharmaceuticals LLC
Category: prescription | Type: HUMAN PRESCRIPTION DRUG LABEL
Date: 20140120

ACTIVE INGREDIENTS: NYSTATIN 500000 [USP'U]/1 1
INACTIVE INGREDIENTS: ANHYDROUS LACTOSE; CARNAUBA WAX; STARCH, CORN; FD&C BLUE NO. 2; FD&C RED NO. 40; HYDROXYPROPYL CELLULOSE (TYPE H); HYPROMELLOSES; MAGNESIUM STEARATE; CELLULOSE, MICROCRYSTALLINE; POLYETHYLENE GLYCOLS; POVIDONES; STARCH, POTATO; STEARIC ACID; TITANIUM DIOXIDE

NYSTATIN TABLETS USP (oral)

Rx only

DESCRIPTION

Nystatin is an antimycotic polyene antibiotic obtained from Streptomyces noursei. Its structural formula:

Nystatin tablets are provided for oral administration as coated tablets containing 500,000 units nystatin.

Inactive ingredients: anhydrous lactose, carnauba wax, corn starch, FD&C Blue No. 2 Aluminum Lake, FD&C Red No. 40 Aluminum Lake, hydroxypropyl cellulose, hypromellose, magnesium stearate, microcrystalline cellulose, polyethylene glycol, povidone, sodium starch glycolate, stearic acid, and titanium dioxide.

CLINICAL PHARMACOLOGY

Pharmacokinetics

Gastrointestinal absorption of nystatin is insignificant. Most orally administered nystatin is passed unchanged in the stool. In patients with renal insufficiency receiving oral therapy with conventional dosage forms, significant plasma concentrations of nystatin may occasionally occur.

Microbiology

Nystatin is both fungistatic and fungicidal in vitro against a wide variety of yeasts and yeast-like fungi. Candida albicans demonstrates no significant resistance to nystatin in vitro on repeated subculture in increasing levels of nystatin; other Candida species become quite resistant. Generally, resistance does not develop in vivo. Nystatin acts by binding to sterols in the cell membrane of susceptible Candida species with a resultant change in membrane permeability allowing leakage of intracellular components. Nystatin exhibits no appreciable activity against bacteria, protozoa, or viruses.

INDICATIONS AND USAGE

Nystatin tablets are intended for the treatment of non-esophageal mucus membrane gastrointestinal candidiasis.

CONTRAINDICATIONS

Nystatin tablets are contraindicated in patients with a history of hypersensitivity to any of their components.

PRECAUTIONS

General

This medication is not to be used for the treatment of systemic mycoses. Discontinue treatment if sensitization or irritation is reported during use.

Carcinogenesis, Mutagenesis, Impairment of Fertility

No long-term animal studies have been performed to evaluate carcinogenic potential. There also have been no studies to determine mutagenicity or whether this medication affects fertility in males or females.

Pregnancy

Teratogenic Effects

Category C

Animal reproduction studies have not been conducted with nystatin. It is also not known whether nystatin can cause fetal harm when administered to a pregnant woman or can affect reproduction capacity. Nystatin should be given to a pregnant woman only if clearly needed.

Nursing Mothers

It is not known whether nystatin is excreted in human milk. Because many drugs are excreted in human milk, caution should be exercised when nystatin is administered to a nursing woman.

ADVERSE REACTIONS

Nystatin is well tolerated even with prolonged therapy. Oral irritation and sensitization have been reported. (See PRECAUTIONS: General.)

Gastrointestinal

Diarrhea (including one case of bloody diarrhea), nausea, vomiting, gastrointestinal upset/disturbances.

Dermatologic

Rash, including urticaria has been reported rarely. Stevens-Johnson syndrome has been reported very rarely.

Other

Tachycardia, bronchospasm, facial swelling, and nonspecific myalgia have also been rarely reported.

OVERDOSAGE

Oral doses of nystatin in excess of five million units daily have caused nausea and gastrointestinal upset. There have been no reports of serious toxic effects of superinfections (see CLINICAL PHARMACOLOGY, Pharmacokinetics).

DOSAGE AND ADMINISTRATION

The usual therapeutic dosage is one to two tablets (500,000 to 1,000,000 units nystatin) three times daily. Treatment should generally be continued for at least 48 hours after clinical cure to prevent relapse.

HOW SUPPLIED

Nystatin tablets, USP 500,000 units, are round, brown, film coated, debossed MP 83. Available as follows:

Bottles of 30 | NDC 33261-0896-30

STORAGE AND HANDLING

Store at 20° to 25°C (68° to 77°F).

[See USP Controlled Room Temperature]

DISPENSE IN TIGHT, LIGHT-RESISTANT CONTAINER.

Manufactured by:
MUTUAL PHARMACEUTICAL COMPANY, INC.
Philadelphia, PA 19124 USA

Repackaged By :
Aidarex Pharmaceuticals LLC,
Corona, CA 92880

Rev 01, July 2009

PRINCIPAL DISPLAY PANEL - 30 Tablet Bottle

NDC 33261-0896-30

NYSTATIN TABLETS USP
(ORAL)

500,000 units

30 TABLETS
Rx only

MUTUAL PHARMACEUTICAL CO., INC.
PHILADELPHIA, PA 19124 USA

Repackaged By :
Aidarex Pharmaceuticals LLC,
Corona, CA 92880